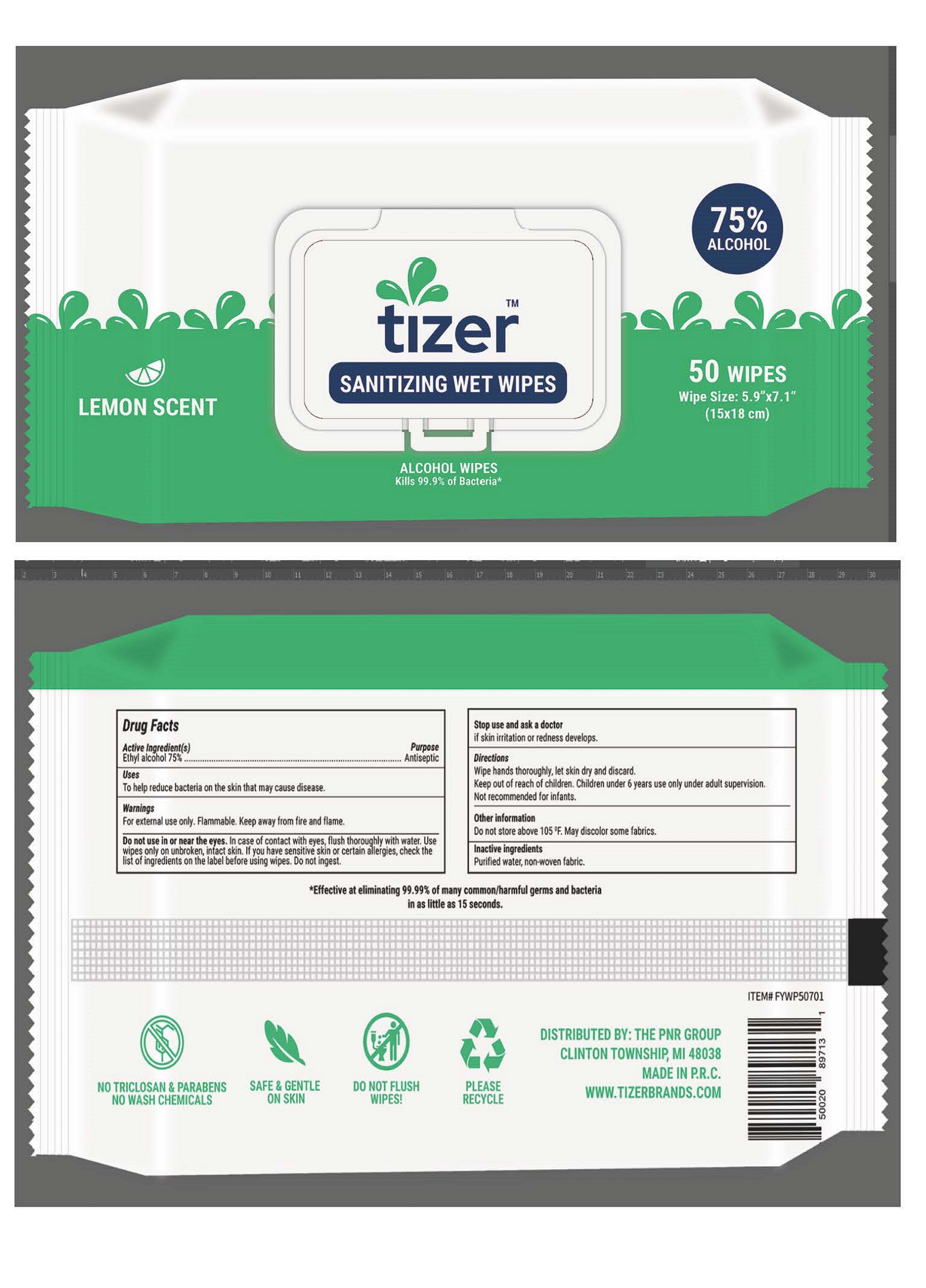 DRUG LABEL: ALCOHOL WIPES
NDC: 11749-050 | Form: CLOTH
Manufacturer: Pnr Group, LLC
Category: otc | Type: HUMAN OTC DRUG LABEL
Date: 20200827

ACTIVE INGREDIENTS: ALCOHOL 75 mL/100 1
INACTIVE INGREDIENTS: WATER

11749-050-50 ALCOHOL WIPES FuYang YangYang Health Technology Co. Ltd

Active Ingredient(s)

Alcohol 75% v/v. Purpose: Antiseptic

Purpose

Antiseptic, Sanitizing wet wipes

Use

to help reduce bacteria on the skin that may cause disease.

Warnings

For external use only. Flammable. Keep away from fire and flame.

Do not use in or near the eyes. In case of contact with eyes, flush thoroughly with water. Use wipes only on unbroken, intact skin. If you have sensitive skin or certain allergies, check the list of ingredients on the label before using wipes. Do not ingest.

When using this product keep out of eyes, ears, and mouth. In case of contact with eyes, rinse eyes thoroughly with water.
Stop use and ask a doctor if irritation or rash occurs. These may be signs of a serious condition.
Keep out of reach of children. If swallowed, get medical help or contact a Poison Control Center right away.

Stop use and ask a doctor if skin irritation or redness develops.

Keep out of reach of children. If swallowed, get medical help or contact a Poison Control Center right away.

Directions

Wipe hands thoroughly, let skin dry and discard.

Keep out of reach of children. Children under 6 years use only under adult supervision.

Not recommended for infants.

Other information

Do not store above 105 ℉. May discolor some fabrics.

Inactive ingredients

purified water USP

Package Label - Principal Display Panel

50 WIPES NDC: 11749-050-50